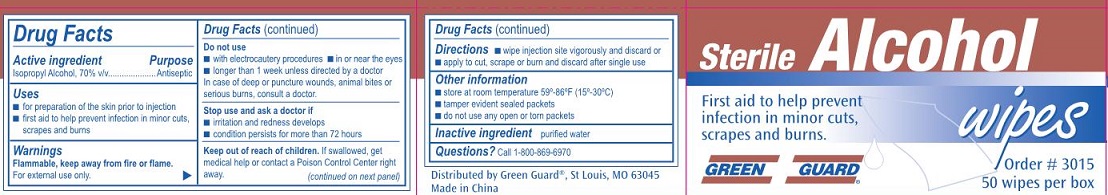 DRUG LABEL: Green Guard Sterile Alcohol Wipes
NDC: 47682-035 | Form: SWAB
Manufacturer: Unifirst First Aid Corporation
Category: otc | Type: HUMAN OTC DRUG LABEL
Date: 20250908

ACTIVE INGREDIENTS: ISOPROPYL ALCOHOL 0.7 mL/1 mL
INACTIVE INGREDIENTS: WATER

Green Guard Sterile Alcohol Wipes

Drug Facts

Active ingredient

Isopropyl Alcohol, 70% v/v

Purpose

Antiseptic

Uses

- for preparation of skin prior to injection
- first aid to help prevent infection in minor cuts, scrapes and burns

Warnings

Flammable, keep away from fire or flame.

For external use only.

Do not use

- with electrocautery procedures
- in or near the eyes
- longer than 1 week unless directed by a doctor

In case of deep or puncture wounds, animal bites or serious burns, consult a doctor.

Stop use and ask a doctor if

- irritation and redness develops
- condition persists for more than 72 hours

Keep out of reach of children.

If swallowed, get medical help or contact a Poison Control Center right away.

Directions

- wipe injection site vigorously and discard or
- apply to cut, scrape or burn and discard after single use

Other information

- store at room temperature 59°-86°F (15°-30°C)

Inactive ingredients

purified water

Questions?

Call 1-800-869-6970

Green Guard Sterile Alcohol Wipes Label

Sterile Alcohol wipes

First aid to help prevent

infection in minor cuts,

scrapes and burns.

Green Guard®

Order # 3015

50 wipes per box